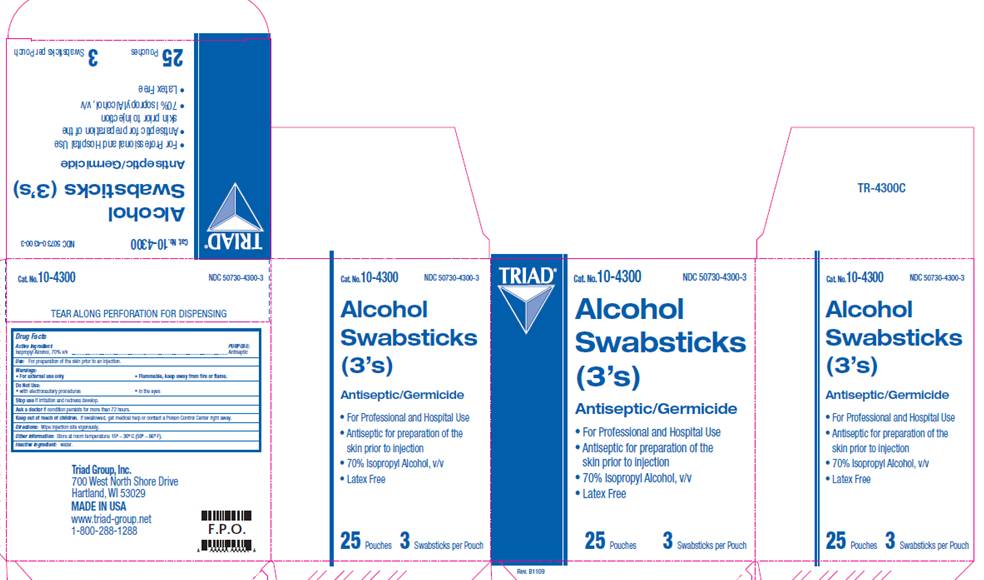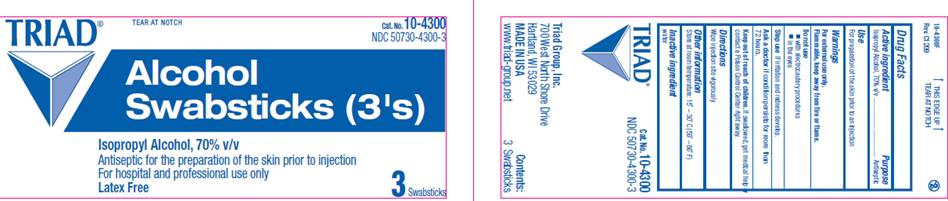 DRUG LABEL: Isopropyl alcohol Swabsticks
NDC: 50730-4300 | Form: LIQUID
Manufacturer: H and P Industries, Inc. dba Triad Group
Category: otc | Type: HUMAN OTC DRUG LABEL
Date: 20091202

ACTIVE INGREDIENTS: Isopropyl alcohol .7 mL/1 mL
INACTIVE INGREDIENTS: water

DRUG FACTS

ACTIVE INGREDIENT

Isopropyl Alcohol 70% v/v

PURPOSE

Antiseptic

USE

- For preparation of the skin prior to injection

WARNINGS

- For external use only

- Flammable, keep away from fire or flame

Do not use

- With electrocautery procedures
- In the eyes

Ask a doctor

if condition persists for more than 72 hours

Stop use

if irritation and redness develop.

KEEP OUT OF REACH OF CHILDREN

If swallowed, get medical help or contact a Poison Control Center right away.

DIRECTIONS

Wipe injection site vigorously

OTHER INFORMATION

Store at room temperature: 15°- 30° C (59° - 86° F)

INACTIVE INGREDIENT

water

POUCH INFORMATION

TRIAD
Cat. No. 10-4300
NDC 50730-4300-3
Alcohol
Swabsticks (3's)
Isopropyl Alcohol, 70% v/v
Antiseptic for the preparation of the skin prior to injection
For Hospital and Professional use only
Latex Free
Triad Group, Inc.
700 West North Shore Drive
Hartland, WI 53029 USA
www.triad-group.net
3 Swabsticks

CARTON INFORMATION

TRIAD
Cat. No. 10-4300
NDC 50730-4300-3
Alcohol
Swabsticks
(3's)

- For Hospital and Professional use
- Antiseptic for the preparation of the skin prior to injection
- Isopropyl Alcohol, 70% v/v
- Latex Free

25 Pouches
3 Swabsticks per Pouch